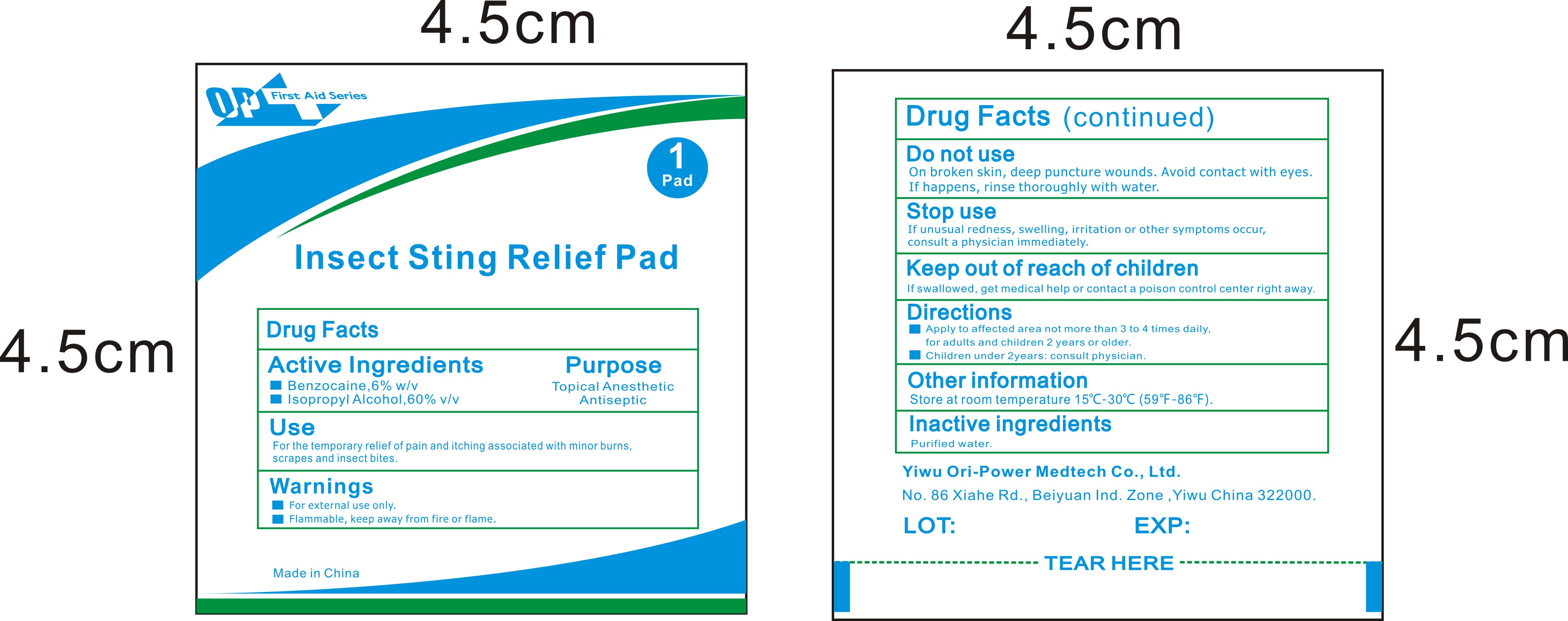 DRUG LABEL: OP First Aid Series Insect Sting Relief Pad
NDC: 72459-013 | Form: CLOTH
Manufacturer: Yiwu Ori-Power Medtech Co.,Ltd.
Category: otc | Type: HUMAN OTC DRUG LABEL
Date: 20260101

ACTIVE INGREDIENTS: BENZOCAINE 60 mg/1 mL; ISOPROPYL ALCOHOL 0.6 mL/1 mL
INACTIVE INGREDIENTS: WATER; SODIUM BICARBONATE

OP First Aid Series Insect Sting Relief Pad

Active Ingredients

Benzocaine,6% w/v

Isopropyl Alcohol,60% v/v

Purpose

Topical Anesthetic

Antiseptic

Use

For the temporary relief of pain and itching associated with minor burns, scrapes and insect bites.

Warnings

- For external use only.

Do not use

On broken skin,deep puncture wounds.Avoid contact with eyes. If happens,rinse thoroughly with water.

Stop use

If unusual redness,swelling,irritation or other symptoms occur,consult a physician immediately.

Keep out of reach of children

If swallowed,get medical help or contact a poison control center right away.

Directions

- Apply to affected area not more than 3 to 4 times daily. for adults and children 2 years or older.
- Children under 2years:consult physician.

Other information

Store at room temperature 15°C-30°C (59°F-86°F).

Inactive ingredients

Purified water,Sodium Bicarbonate.